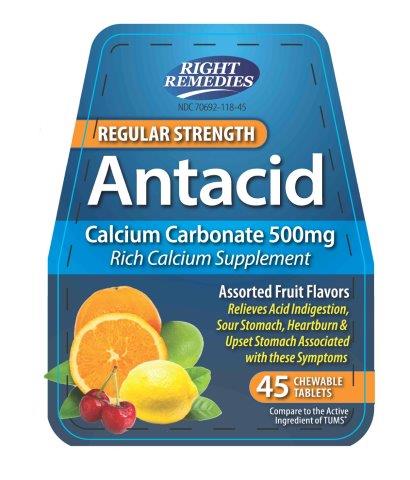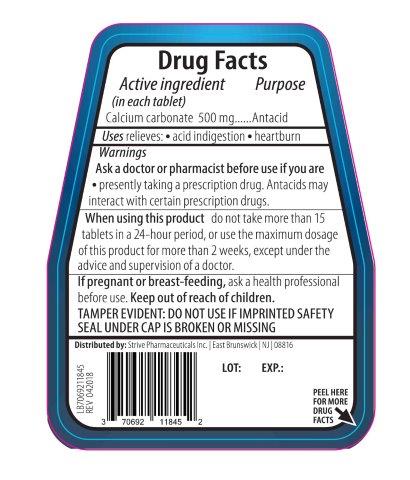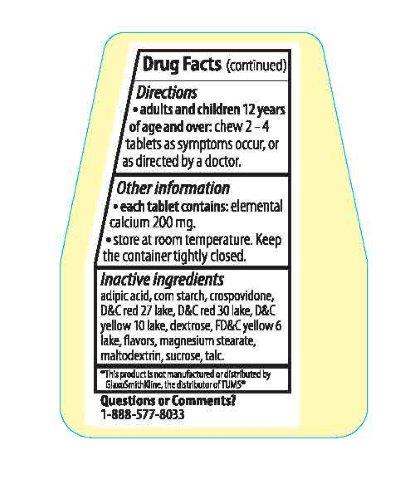 DRUG LABEL: ANTACID REGULAR STRENGTH
NDC: 70692-118 | Form: TABLET, CHEWABLE
Manufacturer: Strive Pharmaceuticals Inc.
Category: otc | Type: HUMAN OTC DRUG LABEL
Date: 20201014

ACTIVE INGREDIENTS: CALCIUM CARBONATE 500 mg/1 1
INACTIVE INGREDIENTS: MAGNESIUM STEARATE; ADIPIC ACID; MODIFIED CORN STARCH (1-OCTENYL SUCCINIC ANHYDRIDE); CROSPOVIDONE; MALTODEXTRIN; D&C RED NO. 30; D&C YELLOW NO. 10; FD&C YELLOW NO. 6; DEXTROSE; D&C RED NO. 27; TALC; SUCROSE

ANATACID REGULAR STRENGTH
Calcium Carbonate 500mg

ACTIVE INGREDIENT

Sennosides USP 15mg

INACTIVE INGREDIENT

adipic acid, corn starch, crospovidone, D&C red 27 lake, D&C red 30 lake, D&C yellow 10 lake, dextrose, FD&C yellow 6 lake, flavors, magnesium stearate, maltodextrin, sucrose, talc.

DOSAGE AND ADMINISTRATION

Adults and children 12 years of age and over: chew 2-4 tablets as symptoms occur, or as directed by a doctor.

INDICATIONS AND USAGE

Relieves:

- acid indigestion
- heartburn

Ask a doctor or Pharmacist before use if you are presently taking a prescription drug. Antacids may interact with certain prescription drugs.

When using this product do not take more than 15 tablets in a 24-hour period, or use the maximum dosage of this product for more than 2 weeks, except under the advice and supervision of a doctor.

If pregnant or breast-feeding,ask a health professional before use.

Keep out of reach of children.

Keep out of reach of children.

PURPOSE

Antacid

OTHER SAFETY INFORMATION

* Each tablet contains: elemental calcium 200mg.

* Store at room temperature. Keep the container tightly closed.